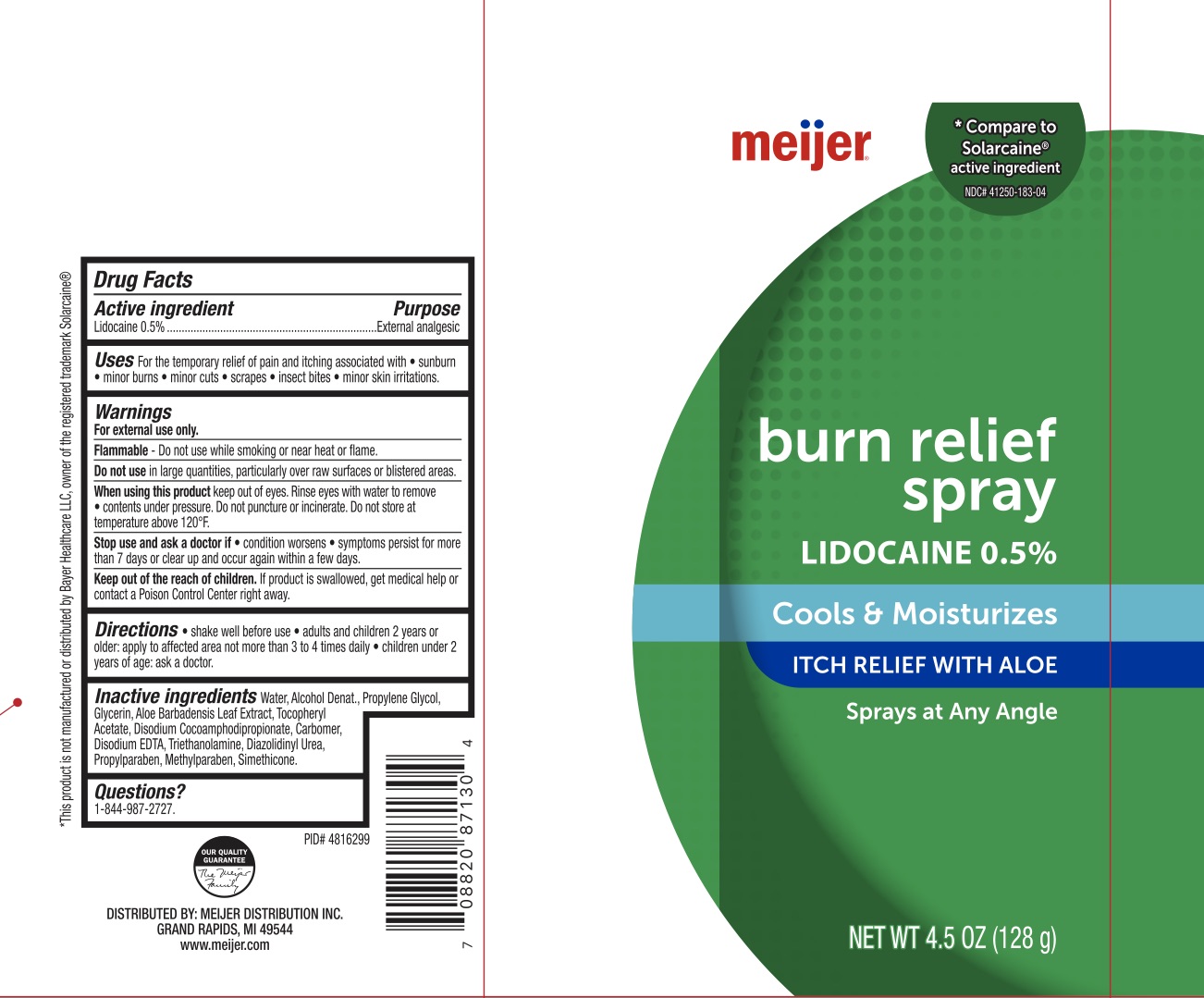 DRUG LABEL: Meijer Burn Relief
NDC: 79481-2183 | Form: SPRAY
Manufacturer: Meijer
Category: otc | Type: HUMAN OTC DRUG LABEL
Date: 20241215

ACTIVE INGREDIENTS: LIDOCAINE 0.5 g/100 g
INACTIVE INGREDIENTS: PROPYLPARABEN; METHYLPARABEN; PROPYLENE GLYCOL; WATER; GLYCERIN; ALOE VERA LEAF; ALCOHOL; DISODIUM COCOAMPHODIPROPIONATE; CARBOMER 940; EDETATE DISODIUM; TROLAMINE; DIAZOLIDINYL UREA; .ALPHA.-TOCOPHEROL ACETATE

Burn Relief Spray

ACTIVE INGREDIENT

Lidocaine 0.5%

PURPOSE

External Analgesic

INDICATIONS AND USAGE

For the temporary relief of pain and itching associated with sunburn, minor burns, minor cuts, scrapes, insect bites, and minor skin irritations.

WARNINGS

For external use only. Flammable--Keep away from fire or flame. Do not use in large quantities, particularly over raw surfaces or blistered areas. When using this product avoid contact with eyes. In case of contact with eyes, flush thoroughly with water, do not apply to wounds or damaged skin, and do not bandage tightly, do not use with a heating pad. Contents under pressure. Do not puncture or incinerate. Do not store at temperature above 120F. . Stop use and ask a doctor if condition worsens, if symptoms persist for more than 7 days or clear up and occur again within a few days.

KEEP OUT OF REACH OF CHILDREN

If swallowed, get medical help or contact a Poison Control Center right away.

DOSAGE AND ADMINISTRATION

Shake well before use. Adults and children 12 years of age and older, apply to the affected area not more than 3 to 4 times daily. Children under 12 years of age: ask a doctor.

INACTIVE INGREDIENT

Water, Alcohol Denat., Propylene Glycol, Glycerin, Aloe Barbadnesis Leaf Extract, Tocopheryl Acetate, Disodium Cocoamphodipropionate, Carbomer, Disodium EDTA, Triethanolamine, Diazolidinyl Urea, Propylparaben, Methylparaben, Simethicone.